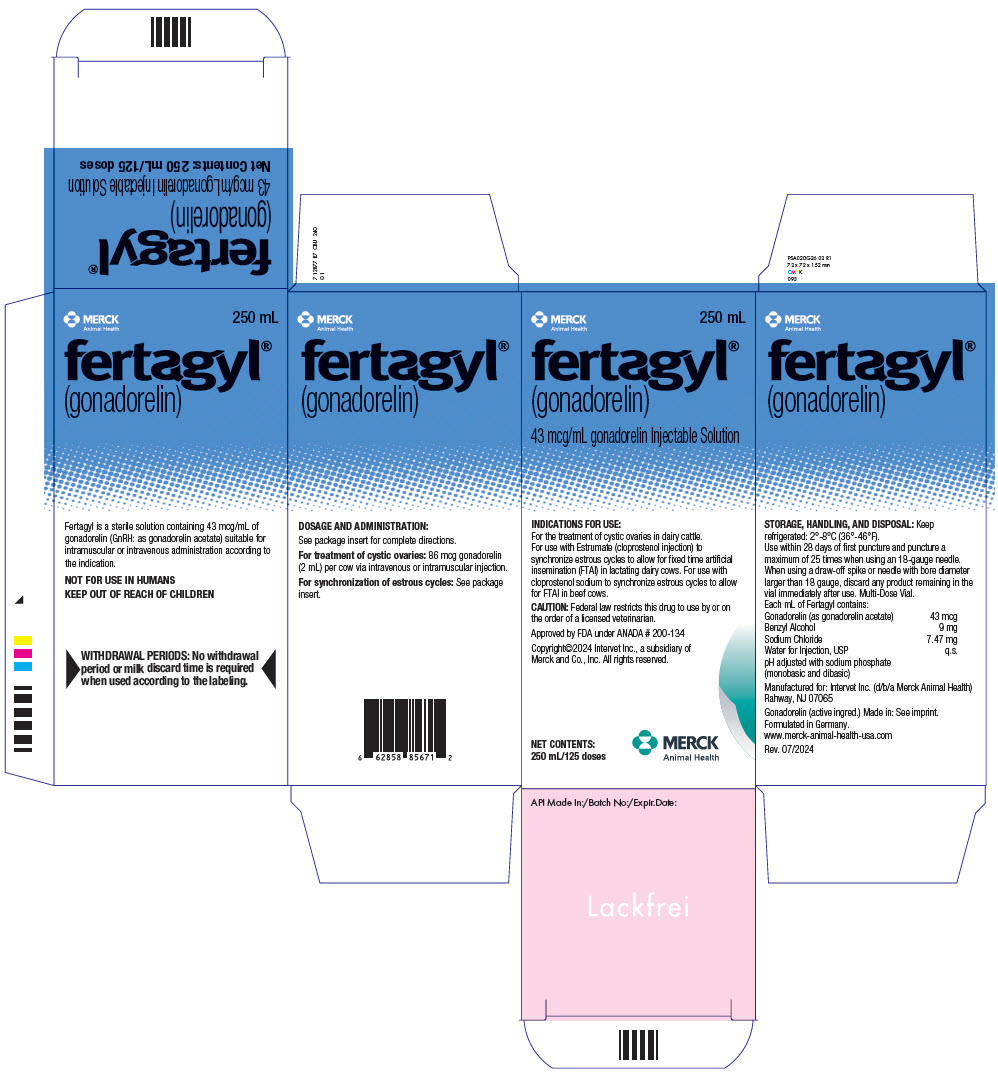 DRUG LABEL: Fertagyl
NDC: 57926-477 | Form: INJECTION
Manufacturer: Merck Sharp & Dohme Corp.
Category: animal | Type: PRESCRIPTION ANIMAL DRUG LABEL
Date: 20241030

ACTIVE INGREDIENTS: GONADORELIN 43 ug/1 mL

fertagyl®
(gonadorelin)
43 mcg/mL gonadorelin Injectable Solution

909935 R8 INU 240
01

For treatment of cystic ovaries in dairy cattle

For use with Estrumate (cloprostenol injection) to synchronize estrous cycles to allow for fixed time artificial insemination (FTAI) in lactating dairy cows

For use with cloprostenol sodium to synchronize estrous cycles to allow for FTAI in beef cows

PRECAUTIONS

CAUTION:

Federal law restricts this drug to use by or on the order of a licensed veterinarian.

DESCRIPTION:

Fertagyl is a sterile solution containing 43 mcg/mL of gonadorelin (GnRH: as gonadorelin acetate) suitable for intramuscular or intravenous administration according to the indication. Gonadorelin is a decapeptide composed of the sequence of amino acids -

5-oxoPro-His-Trp-Ser-Tyr-Gly-Leu-Arg-Pro-Gly-NH2

a molecular weight of 1182.32 and empirical formula C55H75N17O13.

Each mL of Fertagyl contains:

Gonadorelin (as gonadorelin acetate) | 43 mcg
Benzyl Alcohol | 9 mg
Sodium Chloride | 7.47 mg
Water for Injection, USP | q.s.

pH adjusted with sodium phosphate (monobasic and dibasic).

Gonadorelin is the hypothalamic releasing factor responsible for the release of gonadotropins (e.g., luteinizing hormone [LH], follicle stimulating hormone [FSH]) from the anterior pituitary.

Synthetic gonadorelin is physiologically and chemically identical to the endogenous bovine hypothalamic releasing factor.

INDICATIONS FOR USE:

Cystic Ovaries

Fertagyl is indicated for the treatment of ovarian follicular cysts in dairy cattle. Ovarian cysts are non-ovulated follicles with incomplete luteinization which result in nymphomania or irregular estrus.

Historically, cystic ovaries have responded to an exogenous source of LH such as human chorionic gonadotropin.

Fertagyl initiates release of endogenous LH to cause ovulation and luteinization.

Reproductive Synchrony

Fertagyl is indicated for use with Estrumate (cloprostenol injection) to synchronize estrous cycles to allow for fixed time artificial insemination (FTAI) in lactating dairy cows.

Fertagyl is indicated for use with cloprostenol sodium to synchronize estrous cycles to allow for FTAI in beef cows.

DOSAGE AND ADMINISTRATION:

Cystic Ovaries

The intravenous or intramuscular dosage of Fertagyl is 86 mcg gonadorelin (2 mL) per cow.

Reproductive Synchrony

For lactating dairy cows, the intramuscular dosage of Fertagyl is 86 mcg gonadorelin (2 mL) per cow, used in reproductive synchrony programs similar to the following:

- Administer the first Fertagyl injection (2 mL) on Day 0.
- Administer 2 mL of Estrumate (500 mcg cloprostenol, as cloprostenol sodium) by intramuscular injection 6 to 8 days after the first Fertagyl injection.
- Administer the second Fertagyl injection (2 mL) 30 to 72 hours after the Estrumate injection.
- Perform FTAI 8 to 24 hours after the second Fertagyl injection, or inseminate cows on detected estrus using standard herd practices.

For beef cows, the intramuscular dosage of Fertagyl is 86 mcg gonadorelin (2 mL) per cow, used in reproductive synchrony programs similar to the following:

- Administer the first Fertagyl injection (2 mL) on Day 0.
- Administer 500 mcg cloprostenol (as cloprostenol sodium) by intramuscular injection 6 to 8 days after the first Fertagyl injection.
- Administer the second Fertagyl injection (2 mL) 30 to 72 hours after the cloprostenol sodium injection.
- Perform FTAI 0 to 24 hours after the second Fertagyl injection, or inseminate cows on detected estrus using standard herd practices.

WARNINGS

WARNING AND PRECAUTIONS:

Not for use in humans. Keep out of reach of children.

WITHDRAWAL PERIODS:

No withdrawal period or milk discard time is required when used according to the labeling.

To report suspected adverse drug events, for technical assistance or to obtain a copy of the Safety Data Sheet (SDS), contact Intervet at 1-800-211-3573. For additional information about adverse drug experience reporting for animal drugs, contact FDA at 1-888-FDA-VETS, or http://www.fda.gov/reportanimalae

PHARMACOLOGY AND TOXICOLOGY:

Endogenous gonadorelin is synthesized and/or released from the hypothalamus during various stages of the bovine estrous cycle following appropriate neurogenic stimuli. It passes via the hypophyseal portal vessels, to the anterior pituitary to effect the release of gonadotropins (e.g., LH, FSH). Synthetic gonadorelin administered intravenously or intramuscularly also causes the release of endogenous LH or FSH from the anterior pituitary. Gonadorelin acetate has been shown to be safe. The LD50 for mice and rats is greater than 60 mg/kg, and for dogs, greater than 600 mcg/kg, respectively. No adverse effects were noted among rats or dogs administered 120 mcg/kg/day or 72 mcg/kg/day intravenously for 15 days.

It had no adverse effects on heart rate, blood pressure, or EKG to unanesthetized dogs at 60 mcg/kg. In anesthetized dogs it did not produce depression of myocardial or system hemodynamics or adversely affect coronary oxygen supply or myocardial oxygen requirements.

The intravenous administration of 60 mcg/kg/day of gonadorelin acetate to pregnant rats and rabbits during organogenesis did not cause embryotoxic or teratogenic affects.

Further, gonadorelin acetate did not cause irritation at the site of intramuscular administration in dogs with a dose of 72 mcg/kg/day administered for seven (7) days.

TARGET ANIMAL SAFETY:

In addition to the animal safety information presented in the PHARMACOLOGY AND TOXICOLOGY section, the safety of gonadorelin was established through the review and evaluation of the extensive published literature available for the use of gonadorelin-containing products.

The intramuscular administration of 860 mcg gonadorelin (as gonadorelin acetate) on five (5) consecutive days to normally cycling dairy cattle had no effect on hematology or clinical chemistries.

In field studies evaluating the effectiveness of gonadorelin for the treatment of ovarian follicular cysts, the incidence of health abnormalities was not significantly greater in cows administered gonadorelin than cows administered a placebo injection.

The target animal safety of, and injection site reactions to, Fertagyl when used with Estrumate (cloprostenol injection) were evaluated during the conduct of effectiveness field studies in lactating dairy cows. The incidence of health abnormalities was not significantly greater in cows administered Fertagyl than cows administered a placebo injection.

The target animal safety of, and injection site reactions to, gonadorelin when used with cloprostenol sodium were evaluated during the conduct of effectiveness field studies in beef cows. The incidence of health abnormalities was not significantly greater in cows administered gonadorelin than cows administered a placebo injection.

EFFECTIVENESS:

The use of gonadorelin for treatment of ovarian follicular cysts in dairy cattle was demonstrated to be effective with a treatment dose of 86 mcg gonadorelin (as gonadorelin acetate).

The effectiveness of Fertagyl for use with Estrumate (clopostenol injection) to synchronize estrous cycles to allow for FTAI in lactating dairy cows was demonstrated in a field study at six different locations in the U.S. A total of 758 healthy, non-pregnant, primiparous or multiparous lactating dairy cows within 50-120 days postpartum were enrolled in the study. A total of 377 cows were administered Fertagyl (2 mL; 86 mcg gonadorelin as the acetate salt) and 381 cows were administered an equivalent volume of saline as an intramuscular injection twice in the following regimen:

Day 0: 2 mL Fertagyl or saline
Day 7: 2 mL Estrumate (cloprostenol injection)
Day 9: 2 mL Fertagyl or saline

Fixed time AI was performed on Day 10, 16 ± 8 hours after the Day 9 injection. Cows were evaluated for pregnancy on Day 45 ± 5 days by trans-rectal ultrasound or rectal palpation. Pregnancy rate to FTAI was significantly higher (P=0.0051) in cows treated with Fertagyl (33.4%) than the pregnancy rate to FTAI in cows treated with saline (17.8%).

The effectiveness of gonadorelin for use with cloprostenol sodium to synchronize estrous cycles to allow for FTAI in beef cows was demonstrated in a field study at 10 different locations in the U.S. A total of 706 healthy, non-pregnant, primiparous or multiparous beef cows within 40-150 days postpartum were enrolled in the study. A total of 364 cows were administered gonadorelin (1 mL; 100 mcg gonadorelin as the acetate salt) and 342 cows were administered an equivalent volume of water for injection as an intramuscular injection twice in the following regimen:

Day 0: 100 mcg gonadorelin (as the acetate salt) or sterile water for injection
Day 7: 500 mcg cloprostenol (as cloprostenol sodium)
Day 9: 100 mcg gonadorelin (as the acetate salt) or sterile water for injection

Fixed time AI was performed immediately after the Day 9 injection. Cows were evaluated for pregnancy on Day 55±5 days by trans-rectal ultrasound.

Pregnancy rate to FTAI was significantly higher (P=0.0006) in cows treated with gonadorelin (21.7%) than the pregnancy rate to FTAI in cows treated with water (7.4%).

The effectiveness of a 2-mL dose of gonadorelin delivering 86 mcg gonadorelin (as gonadorelin acetate) for use with cloprostenol sodium to synchronize estrous cycles to allow for FTAI in lactating dairy cows and beef cows was also demonstrated through references to scientific literature.

HOW SUPPLIED:

Fertagyl is available in a concentration of 43 mcg/mL gonadorelin (as gonadorelin acetate) pH adjusted with sodium phosphate (monobasic and dibasic). Fertagyl is supplied in multi-dose vials containing 20 mL, 100 mL, and 250 mL of sterile solution.

STORAGE AND HANDLING

STORAGE, HANDLING, AND DISPOSAL: Keep refrigerated: 2°-8°C (36°-46°F).

20-mL vial: Use within 28 days of first puncture.

100-mL vial: Use within 28 days of first puncture and puncture a maximum of 10 times when using an 18-gauge needle. When using a draw-off spike or needle with bore diameter larger than 18 gauge, discard any product remaining in the vial immediately after use.

250-mL vial: Use within 28 days of first puncture and puncture a maximum of 25 times when using an 18-gauge needle. When using a draw-off spike or needle with bore diameter larger than 18 gauge, discard any product remaining in the vial immediately after use.

Approved by FDA under ANADA # 200-134

Manufactured for:
Intervet Inc. (d/b/a Merck Animal Health)
Rahway, NJ 07065
Formulated in Germany.

Copyright©2024 Intervet Inc. (d/b/a Merck Animal Health), a subsidiary of Merck and Co., Inc. All rights reserved.

Rev. 07/2024

PRINCIPAL DISPLAY PANEL - 250 mL Vial Carton

MERCK
Animal Health

250 mL

fertagyl®
(gonadorelin)
43 mcg/mL gonadorelin Injectable Solution

INDICATIONS FOR USE:
For the treatment of cystic ovaries in dairy cattle.
For use with Estrumate (cloprostenol injection) to
synchronize estrous cycles to allow for fixed time artificial
insemination (FTAI) in lactating dairy cows. For use with
cloprostenol sodium to synchronize estrous cycles to allow
for FTAI in beef cows.

CAUTION: Federal law restricts this drug to use by or on
the order of a licensed veterinarian.

Approved by FDA under ANADA # 200-134

Copyright©2024 Intervet Inc., a subsidiary of
Merck and Co., Inc. All rights reserved.

NET CONTENTS:
250 mL/125 doses

MERCK
Animal Health